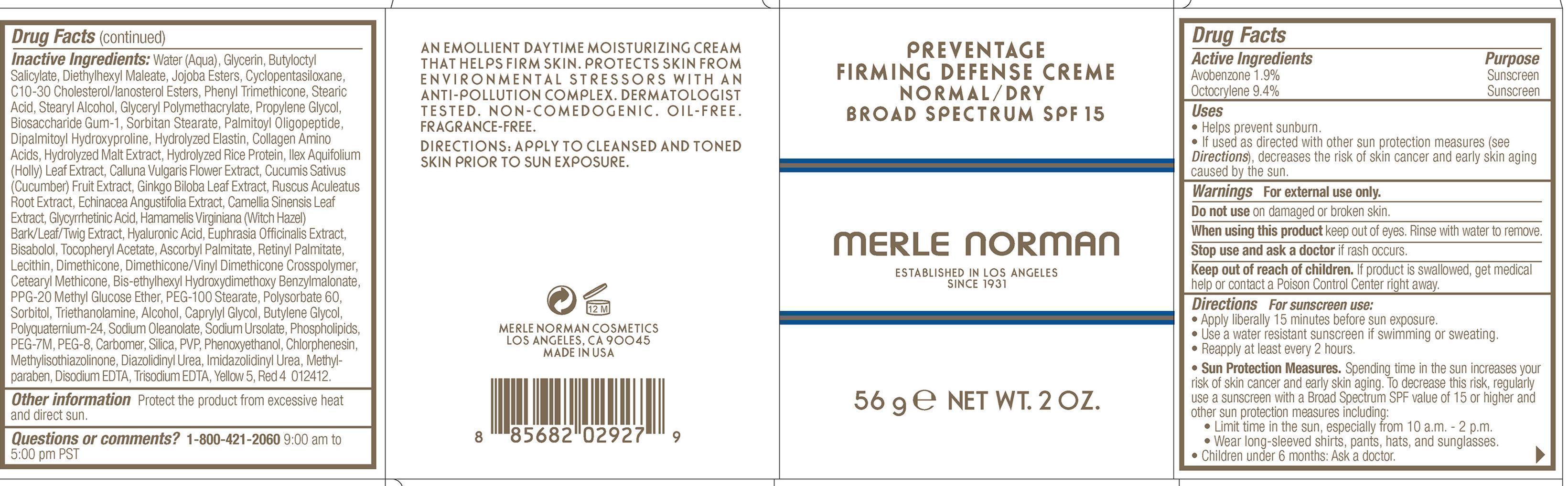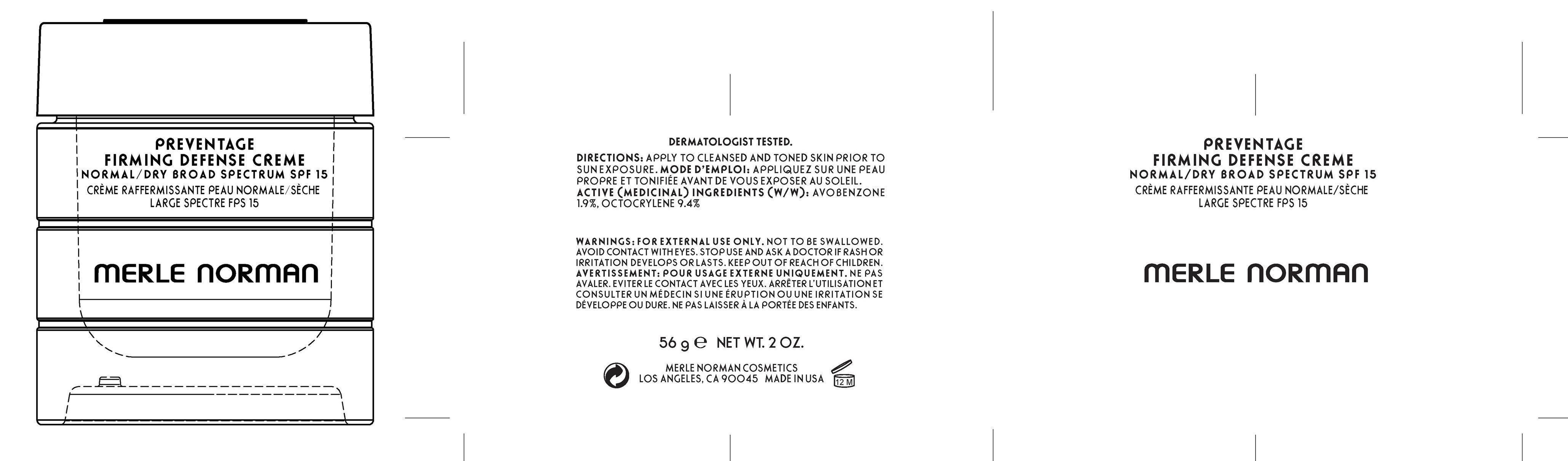 DRUG LABEL: Preventage Firming Defense Creme Normal/Dry
NDC: 57627-121 | Form: CREAM
Manufacturer: Merle Norman Cosmetics, Inc
Category: otc | Type: HUMAN OTC DRUG LABEL
Date: 20200127

ACTIVE INGREDIENTS: AVOBENZONE 1.064 g/56 g; OCTOCRYLENE 5.264 g/56 g
INACTIVE INGREDIENTS: WATER; GLYCERIN; BUTYLOCTYL SALICYLATE; DIETHYLHEXYL MALEATE; CYCLOMETHICONE 5; C10-30 CHOLESTEROL/LANOSTEROL ESTERS; PHENYL TRIMETHICONE; STEARIC ACID; STEARYL ALCOHOL; PROPYLENE GLYCOL; BIOSACCHARIDE GUM-1; SORBITAN MONOSTEARATE; PALMITOYL OLIGOPEPTIDE; DIPALMITOYL HYDROXYPROLINE; HYDROLYZED ELASTIN, BOVINE, ALKALINE (1000 MW); ILEX AQUIFOLIUM LEAF; CALLUNA VULGARIS FLOWERING TOP; CUCUMBER; GINKGO; RUSCUS ACULEATUS ROOT; ECHINACEA ANGUSTIFOLIA ROOT; GREEN TEA LEAF; ENOXOLONE; HYALURONIC ACID; EUPHRASIA STRICTA; LEVOMENOL; .ALPHA.-TOCOPHEROL ACETATE; ASCORBYL PALMITATE; VITAMIN A PALMITATE; DIMETHICONE; BIS-ETHYLHEXYL HYDROXYDIMETHOXY BENZYLMALONATE; PPG-20 METHYL GLUCOSE ETHER; PEG-100 STEARATE; POLYSORBATE 60; SORBITOL; TROLAMINE; ALCOHOL; CAPRYLYL GLYCOL; BUTYLENE GLYCOL; SODIUM OLEANOLATE; SODIUM URSOLATE; POLYETHYLENE GLYCOL 300000; POLYETHYLENE GLYCOL 400; SILICON DIOXIDE; PHENOXYETHANOL; CHLORPHENESIN; METHYLISOTHIAZOLINONE; DIAZOLIDINYL UREA; IMIDUREA; METHYLPARABEN; EDETATE DISODIUM; EDETATE TRISODIUM; FD&C YELLOW NO. 5; FD&C RED NO. 4

Merle Norman Preventage Firming Defense Creme Normal/Dry

Active Ingredients Purpose
Avobenzone 1.9% Sunscreen
Octocrylene 9.4% Sunscreen

Uses

-Helps prevent sunburn.

-If used as directed with other sun protection measures (see Directions), decreases the risk of skin cancer and early skin aging caused by the sun.

Keep out of reach of children. If product is swallowed, get medical help or contact a Poison Control Center right away.

Stop use and ask a doctor if rash occurs.

Warnings For external use only.

Do not use on damaged or broken skin.

When using this product keep out of eyes. Rinse with water to remove.

DOSAGE AND ADMINISTRATION

Directions For sunscreen use:

-Apply liberally 15 minutes before sun exposure.

-Use a water resistant sunscreen if swimming or sweating.

-Reapply at least every 2 hours.

Sun Protection Measures. Spending time in the sun increases your risk of sin cancer and early skin aging. To decrease this risk, regularly use a sunscreen with a Broad Spectrum SPF value of 15 or higher and other sun protection measures including:

-Limit time in the sun, especially from 10 a.m. – 2 p.m.

-Wear long-sleeved shirts, pants, hats, and sunglasses.

Children under 6 months: Ask a doctor.

INACTIVE INGREDIENT

Inactive Ingredients: Water (Aqua), Glycerin, Butyloctyl Salicylate, Diethylhexyl Maleate, Jojoba Esters, Cyclopentasiloxane, C10-30 Cholesterol/Lanosterol Esters, Phenyl Trimethicone, Stearic Acid, Stearyl Alcohol, GlycerylPolymethacrylate, Propylene Glycol, Biosaccharide Gum-1, Sorbitan Stearate, PalmitoylOligopeptide, DipalmitoylHydroxylproline, Hydrolyzed Elastin, Collagen Amino Acids, Hydrolyzed Malt Extract, Hydrolyzed Rice Protein, Ilex Aquifolium (Holly) Leaf Extract, Calluna Vulgaris Flower Extract, CucumisSativus (Cucumber) Fruit Extract, Ginkgo Biloba Leaf Extract, RuscusAculeatus Root Extract, Echinacea Angustifolia Extract, Camellia Sinensis Leaf Extract, Glycyrrhetinic Acid, HamamelisVirginiana (Witch Hazel) Bark/Leaf/Twig Extract, Hyaluronic Acid, EuphrasiaOfficinalis Extract, Bisabolol, Tocopheryl Acetate, AscorbylPalmitate, RetinylPalmitate, Lecithin, Dimethicone, Dimethicone/Vinyl DimethiconeCrosspolymer, CetearylMethicone, Bis-EthylhexylHydroxydimethoxyBenzylmalonate, PPG-20 Methyl Glucose Ether, PEG-100 Stearate, Polysorbate 60, Sorbitol, Triethanolamine, Alcohol, Caprylyl Glycol, Butylene Glycol, Polyquaternium-24, Sodium Oleanolate, Sodium Ursolate, Phospholipids, PEG-7M, PEG-8, Carbomer, Silica, PVP, Phenoxyethanol, Chlorphenesin, Methylisothiazolinone, Diazolidinyl Urea, Imidazolidinyl Urea, Methylparaben, Disodium EDTA, Trisodium EDTA, Yellow 5, Red 4

PACKAGE LABEL

Preventage Firming Defense creme

Broad Spectrum SPF 15

Merle Norman established in Los Angeles since 1931

56 g Net Wt. 2 Oz